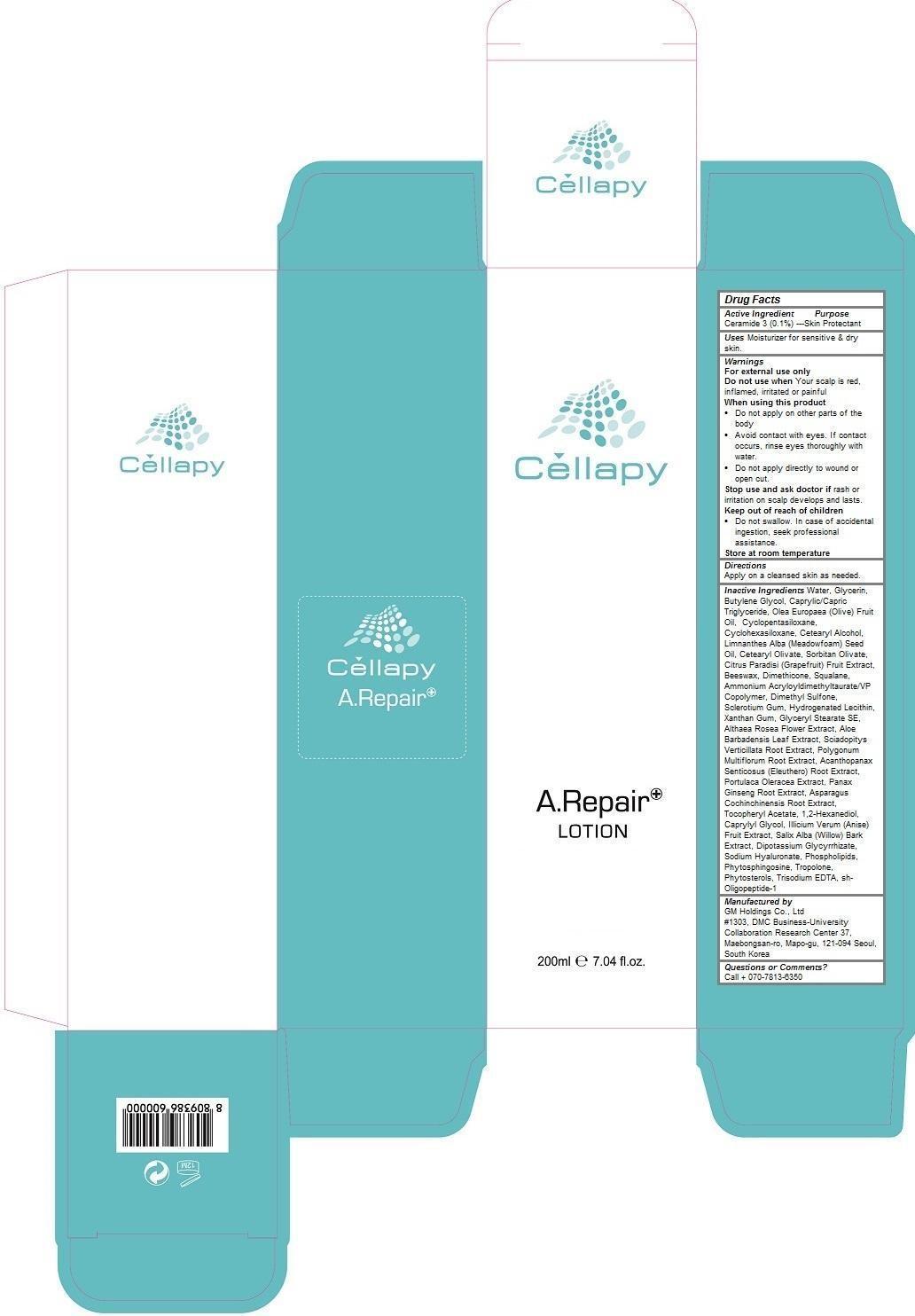 DRUG LABEL: Cellapy A Repair
NDC: 69278-104 | Form: LOTION
Manufacturer: GM Holdings Co., Ltd
Category: otc | Type: HUMAN OTC DRUG LABEL
Date: 20200121

ACTIVE INGREDIENTS: CERAMIDE 3 0.05 1/200 mL
INACTIVE INGREDIENTS: WATER; GLYCERIN; BUTYLENE GLYCOL; MEDIUM-CHAIN TRIGLYCERIDES; OLIVE OIL; CYCLOMETHICONE 5; CETOSTEARYL ALCOHOL; MEADOWFOAM SEED OIL; CETEARYL OLIVATE; SORBITAN OLIVATE; GRAPEFRUIT; YELLOW WAX; DIMETHICONE; SQUALANE; AMMONIUM ACRYLOYLDIMETHYLTAURATE/VP COPOLYMER; DIMETHYL SULFONE; BETASIZOFIRAN; HYDROGENATED SOYBEAN LECITHIN; XANTHAN GUM; GLYCERYL STEARATE SE; ALCEA ROSEA FLOWER; ALOE VERA LEAF; SCIADOPITYS VERTICILLATA ROOT; FALLOPIA MULTIFLORA ROOT; ELEUTHERO; PURSLANE; ASIAN GINSENG; ASPARAGUS COCHINCHINENSIS TUBER; .ALPHA.-TOCOPHEROL ACETATE; 1,2-HEXANEDIOL; CAPRYLYL GLYCOL; STAR ANISE FRUIT; SALIX ALBA BARK; GLYCYRRHIZINATE DIPOTASSIUM; HYALURONATE SODIUM; OMEGA-3 FATTY ACIDS; PHYTOSPHINGOSINE; TROPOLONE; NEPIDERMIN

Cellapy A Repair Lotion